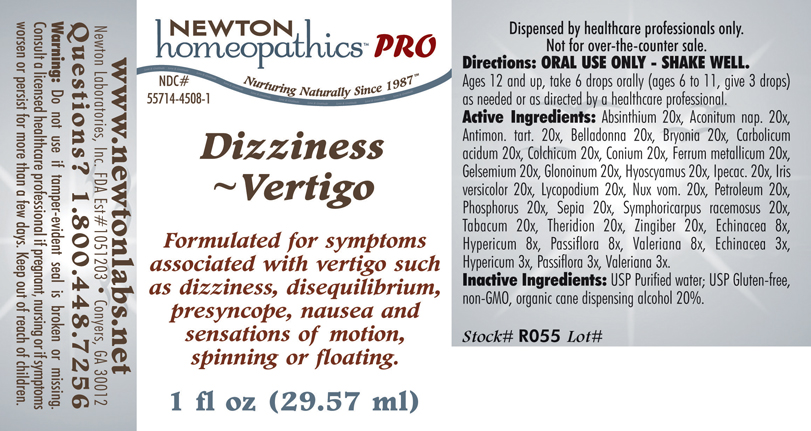 DRUG LABEL: Dizziness  - Vertigo 
NDC: 55714-4508 | Form: LIQUID
Manufacturer: Newton Laboratories, Inc.
Category: homeopathic | Type: HUMAN PRESCRIPTION DRUG LABEL
Date: 20110601

ACTIVE INGREDIENTS: Wormwood 20 [hp_X]/1 mL; Aconitum Napellus 20 [hp_X]/1 mL; Antimony Potassium Tartrate 20 [hp_X]/1 mL; Atropa Belladonna 20 [hp_X]/1 mL; Bryonia Alba Root 20 [hp_X]/1 mL; Phenol 20 [hp_X]/1 mL; Colchicum Autumnale Bulb 20 [hp_X]/1 mL; Conium Maculatum Flowering Top 20 [hp_X]/1 mL; Iron 20 [hp_X]/1 mL; Gelsemium Sempervirens Root 20 [hp_X]/1 mL; Nitroglycerin 20 [hp_X]/1 mL; Hyoscyamus Niger 20 [hp_X]/1 mL; Ipecac 20 [hp_X]/1 mL; Iris Versicolor Root 20 [hp_X]/1 mL; Lycopodium Clavatum Spore 20 [hp_X]/1 mL; Strychnos Nux-vomica Seed 20 [hp_X]/1 mL; Kerosene 20 [hp_X]/1 mL; Phosphorus 20 [hp_X]/1 mL; Sepia Officinalis Juice 20 [hp_X]/1 mL; Symphoricarpos Albus Fruit 20 [hp_X]/1 mL; Tobacco Leaf 20 [hp_X]/1 mL; Theridion Curassavicum 20 [hp_X]/1 mL; Ginger 20 [hp_X]/1 mL; Echinacea, Unspecified 8 [hp_X]/1 mL; Hypericum Perforatum 8 [hp_X]/1 mL; Passiflora Incarnata Flowering Top 8 [hp_X]/1 mL; Valerian 8 [hp_X]/1 mL
INACTIVE INGREDIENTS: Alcohol

Dizziness - Vertigo

INDICATIONS & USAGE SECTION

Dizziness - Vertigo Formulated for symptoms associated with vertigo such as dizziness, disequilibrium, presyncope, nausea and sensations of motion, spinning or floating.

DOSAGE & ADMINISTRATION SECTION

Directions: ORAL USE ONLY - SHAKE WELL. Ages 12 and up, take 6 drops orally (ages 6 to 11, give 3 drops) as needed or as directed by a healthcare professional.

ACTIVE INGREDIENT SECTION

Absinthium 20x, Aconitum nap. 20x, Antimon. tart. 20x, Belladonna 20x, Bryonia 20x, Carbolicum acidum 20x, Colchicum 20x, Conium 20x, Ferrum metallicum 20x, Gelsemium 20x, Glonoinum 20x, Hyoscyamus 20x, Ipecac. 20x, Iris versicolor 20x, Lycopodium 20x, Nux vom. 20x, Petroleum 20x, Phosphorus 20x, Sepia 20x, Symphoricarpus racemosus 20x, Tabacum 20x, Theridion 20x, Zingiber 20x, Echinacea 8x, Hypericum 8x, Passiflora 8x, Valeriana 8x, Echinacea 3x, Hypericum 3x, Passiflora 3x, Valeriana 3x.

PURPOSE SECTION

Formulated for symptoms associated with vertigo such as dizziness, disequilibrium, presyncope, nausea and sensations of motion, spinning or floating.

INACTIVE INGREDIENT SECTION

Inactive Ingredients: USP Purified Water; USP Gluten-free, non-GMO, organic cane dispensing alcohol 20%.

QUESTIONS? SECTION

www.newtonlabs.net Newton Laboratories, Inc. FDA Est # 1051203 - Conyers, GA 30012
Questions? 1.800.448.7256

WARNINGS SECTION

Warning: Do not use if tamper - evident seal is broken or missing. Consult a licensed healthcare professional if pregnant, nursing or if symptoms worsen or persist for more than a few days. Keep out of reach of children.

PREGNANCY OR BREAST FEEDING SECTION

Consult a licensed healthcare professional if pregnant, nursing or if symptoms worsen or persist for more than a few days.

KEEP OUT OF REACH OF CHILDREN SECTION

Keep out of reach of children.